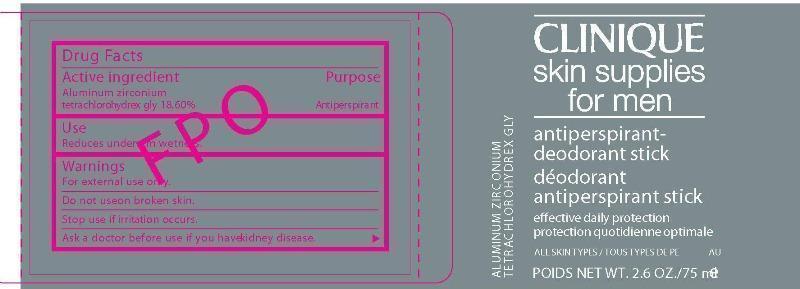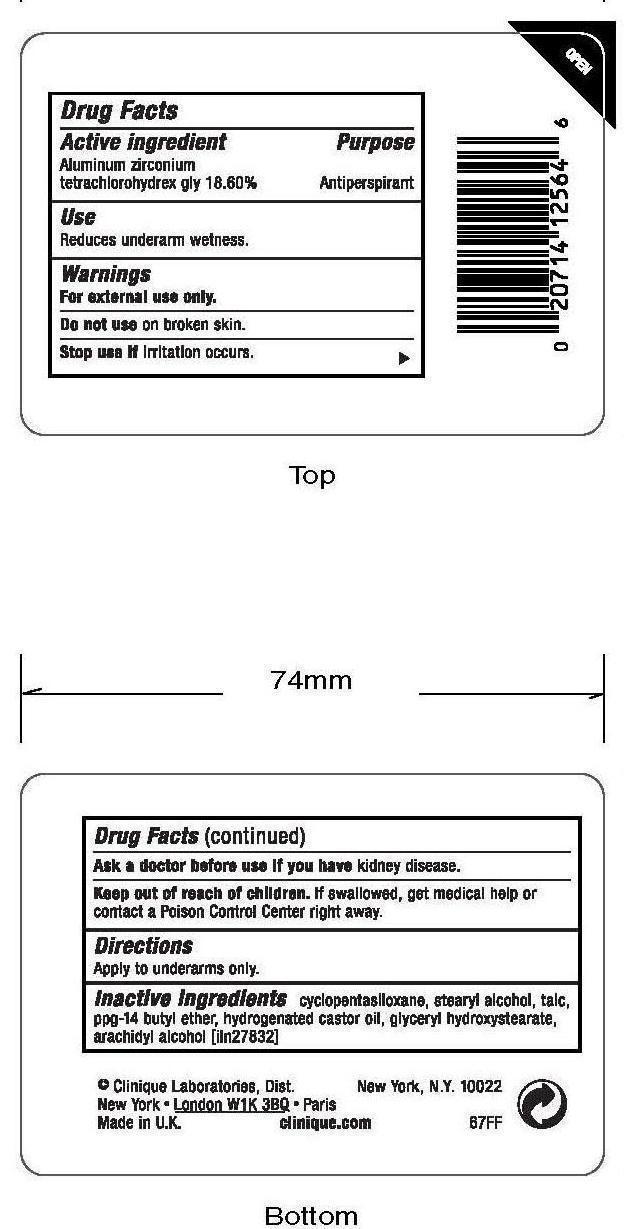 DRUG LABEL: Skin Supplies for Men antiperspirant
NDC: 49527-715 | Form: STICK
Manufacturer:  CLINIQUE LABORATORIES INC 
Category: otc | Type: HUMAN OTC DRUG LABEL
Date: 20150102

ACTIVE INGREDIENTS: ALUMINUM ZIRCONIUM TETRACHLOROHYDREX GLY 18.6 g/100 mL
INACTIVE INGREDIENTS: CYCLOMETHICONE 5; STEARYL ALCOHOL; TALC; PPG-14 BUTYL ETHER; HYDROGENATED CASTOR OIL; ARACHIDYL ALCOHOL

Clinique Skin Supplies for men Antiperspirant

Active ingredients Purpose

Aluminum zirconium tetrachlorohydrex 18.60% Antiperspirant

Use

Reduces underarm wetness

Keep out of reach of children

Stop use if irritation occurs.

Warnings

For external use only.

Do not use on broken skin.

Ask a doctor before use if you have kidney disease.

If swallowed get medical help or contact a poison control center right away.

Directions

apply to underarms only.

INACTIVE INGREDIENT

Inactive ingredients: cyclopentasiloxane, stearyl alcohol, talc, ppg-14 butyl ether, hydrogenated castor oil, glyceryl hydroxystearate, arachidyl alcohol.

PACKAGE LABEL

Clinique

Skin supplies for men

antiperspirant-deodorant stick

Deodorant antiperspirant stick

effective daily protection

protection quotidienne optimale

all skin types/tous types de peau

Poids Net. Wt. 2.6 oz/75 ml